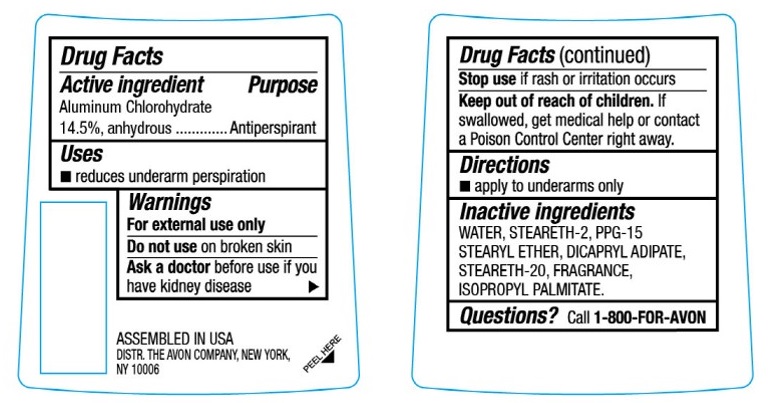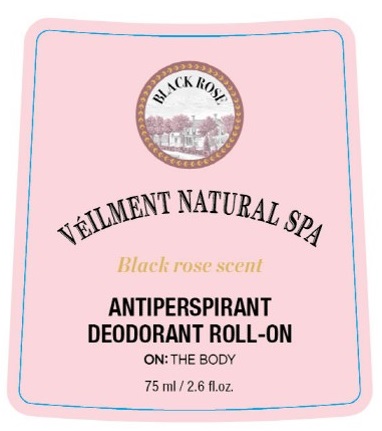 DRUG LABEL: Veilment Natural Spa Black Rose
NDC: 10096-1005 | Form: GEL
Manufacturer: The Avon Company
Category: otc | Type: HUMAN OTC DRUG LABEL
Date: 20210811

ACTIVE INGREDIENTS: ALUMINUM CHLOROHYDRATE 145 mg/1 mL
INACTIVE INGREDIENTS: WATER; DICAPRYL ADIPATE; STEARETH-20; STEARETH-2; PPG-15 STEARYL ETHER; ISOPROPYL PALMITATE

Veilment Natural Spa Black Rose Anti-Perspirant Roll-on Deodorant

Drug Facts

Active Ingredient

Aluminum Chlorohydrate 14.5%, anhydrous

Purpose

Antiperspirant

Uses

- reduces underarm perspiration

Warnings

For external use only

Do not use on broken skin

Ask a doctor before use if you have kidney disease

Stop use if rash or irritation occurs

Keep out of reach of children. If swallowed, get medical help or contact a Poison Control Center right away.

Directions

- apply to underarms only

Inactive Ingredients

WATER, STEARETH-2, PPG-15 STEARYL ETHER, DICAPRYL ADIPATE, STEARETH-20, FRAGRANCE, ISOPROPYL PALMITATE

Questions?

Call 1-800-FOR-AVON

Principal Display Panel

VEILMENT NATURAL SPA
Black Rose scent

ANTI-PERSPIRANT
DEODORANT ROLL-ON

ON: THE BODY
75 ml / 2.6 fl.oz.

ASSEMBLED IN USA
DISTR. THE AVON COMPANY, NEW YORK,
NY 10006